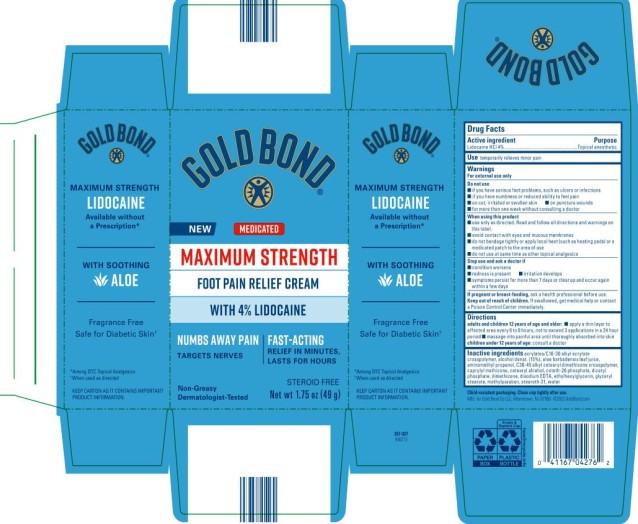 DRUG LABEL: Gold Bond Maximum Strength Foot Pain Relief
NDC: 84714-0427 | Form: CREAM
Manufacturer: Gold Bond Co LLC
Category: otc | Type: HUMAN OTC DRUG LABEL
Date: 20260301

ACTIVE INGREDIENTS: LIDOCAINE HYDROCHLORIDE 4 g/100 g
INACTIVE INGREDIENTS: ACRYLATES/C10-30 ALKYL ACRYLATE CROSSPOLYMER (60000 MPA.S); ALCOHOL; ALOE VERA LEAF; AMINOMETHYLPROPANOL; C30-45 ALKYL CETEARYL DIMETHICONE CROSSPOLYMER; CAPRYLYL METHICONE; CETEARYL ALCOHOL; CETETH-20 PHOSPHATE; DICETYL PHOSPHATE; DIMETHICONE; EDETATE DISODIUM; ETHYLHEXYLGLYCERIN; GLYCERYL STEARATE; METHYLPARABEN; STEARETH-21; WATER

Gold Bond Maximum Strength Foot Pain Relief Cream

Gold Bond® Maximum Strength Foot Pain
Relief Cream with Lidocaine

Drug Facts

Active ingredient

Lidocaine HCl 4%

Purpose

Topical anesthetic

Use

Temporarily relieves minor pain

Warnings

For external use only

Do not use

- if you have serious foot problems, such as ulcers or infections
- if you have numbness or reduced ability to feel pain
- on cut, irritated or swollen skin
- on puncture wounds
- for more than one week without consulting a doctor

When using this product

- use only as directed. Read and follow all directions and warnings on this carton.
- avoid contact with eyes and mucous membranes
- do not bandage tightly or apply local heat (such as heating pads) or a medicated patch to the area of use
- do not use at same time as other topical analgesics

Stop use and ask a doctor if

- condition worsens
- redness is present
- irritation develops
- symptoms persist for more than 7 days or clear up and occur again within a few days

If pregnant or breast-feeding,

ask a health professional before use.

Keep out of reach of children.

If swallowed, get medical help or contact a Poison Control Center immediately.

Directions

adults and children over 12 years:

- apply a thin layer to affected area every 6 to 8 hours, not to exceed 3 applications in a 24 hour period
- massage into painful area until thoroughly absorbed into skin

children under 12 years of age: ask a doctor

Inactive ingredients

acrylates/C10-30 alkyl acrylate crosspolymer, alcohol denat. (15%), aloe barbadensis leaf juice, aminomethyl propanol, C30-45 alkyl cetearyl dimethicone crosspolymer, caprylyl methicone, cetearyl alcohol, ceteth-20 phosphate, dicetyl phosphate, dimethicone, disodium EDTA, ethylhexylglycerin, glyceryl stearate, methylparaben, steareth-21, water

Child resistant packaging. Close cap tightly after use.

PRINCIPAL DISPLAY PANEL

Gold Bond Maximum Strength Foot Pain Relief Cream
Net Wt 1.75 oz (49g)